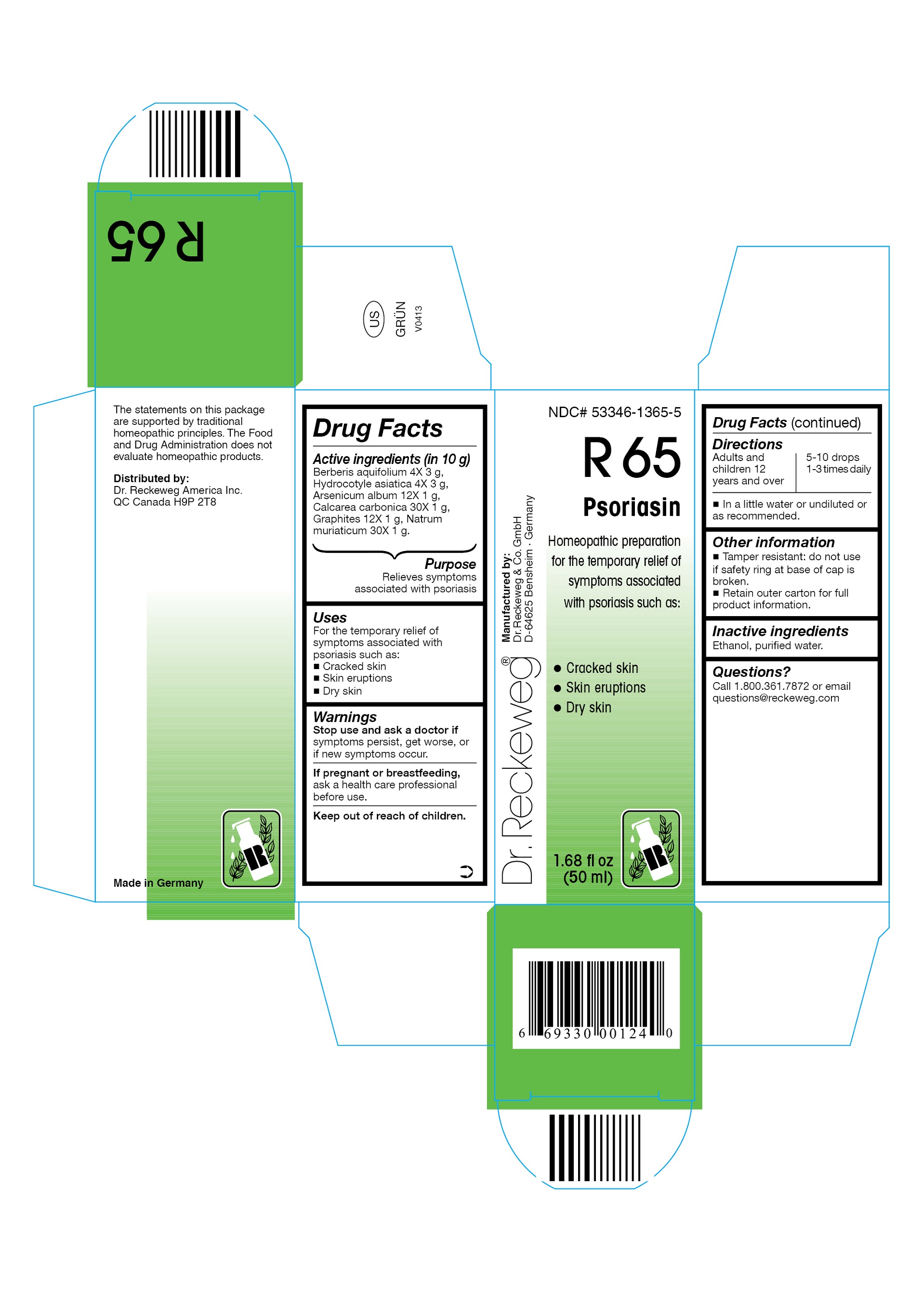 DRUG LABEL: DR. RECKEWEG R65 Psoriasin 
NDC: 53346-1365 | Form: LIQUID
Manufacturer: PHARMAZEUTISCHE FABRIK DR. RECKEWEG & CO
Category: homeopathic | Type: HUMAN OTC DRUG LABEL
Date: 20130404

ACTIVE INGREDIENTS: MAHONIA AQUIFOLIUM WHOLE 4 [hp_X]/50 mL; CENTELLA ASIATICA 4 [hp_X]/50 mL; ARSENIC TRIOXIDE 12 [hp_X]/50 mL; OYSTER SHELL CALCIUM CARBONATE, CRUDE 30 [hp_X]/50 mL; GRAPHITE 12 [hp_X]/50 mL; SODIUM CHLORIDE 30 [hp_X]/50 mL
INACTIVE INGREDIENTS: ALCOHOL; WATER

DR. RECKEWEG R65 Psoriasin

Active ingredients

Berberis aquifolium 4X 3 g, Hydrocotyle asiatica 4X 3 g, Arsenicum album 12X 1 g, Calcarea carbonica 30X 1 g, Graphites 12X 1 g, Natrum muriaticum 30X 1 g in 10 g.

Purpose

Relieves symptoms associated with psoriasis

Uses

For the temporary relief of symptoms associated with psoriasis such as:

- Cracked skin
- Skin eruptions
- Dry skin

Warnings

Stop use and ask a doctor if symptoms persist, get worse, or if new symptoms occur.

PREGNANCY OR BREAST FEEDING

If pregnant or breastfeeding, ask a health care professional before use.

Keep out of reach of children.

Directions
Adults and children ≥ 12 years 5-10 drops 1-3 times daily in a little water or undiluted or as recommended.

Other information

- Tamper resistant: do not use if safety ring at base of cap is broken.
- Retain outer carton for full product information.

Inactive ingredients
Ethanol, purified water.

Questions?
Call 1-800-361-7872 or email questions@reckeweg.com

PACKAGE LABEL

NDC# 53346-1365-5
Dr. Reckeweg R65 Psoriasin
Homeopathic preparation for the temporary relief of symptoms associated with psoriasis such as:

- Cracked skin
- Skin eruptions
- Dry skin

Manufactured by:
Dr. Reckeweg Co. GmbH
D-64625 Bensheim
Germany
1.68 fl oz
(50 ml)